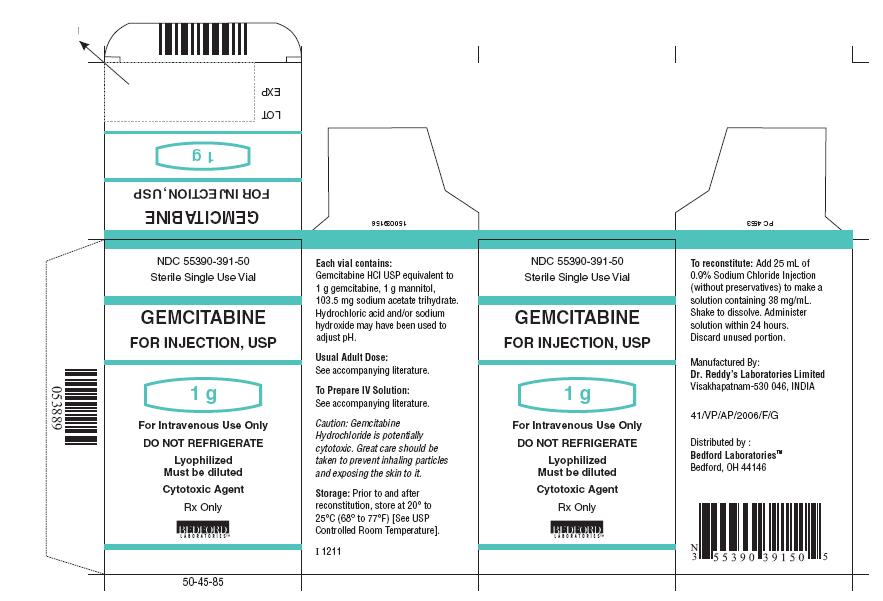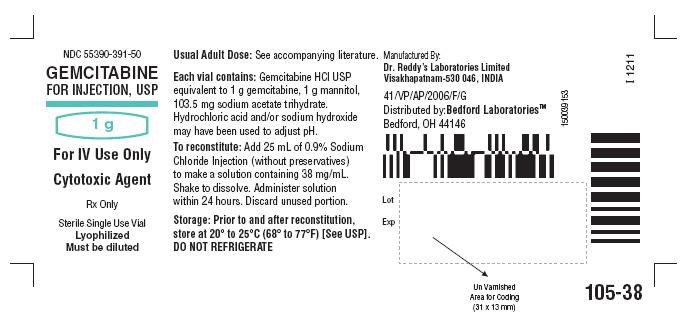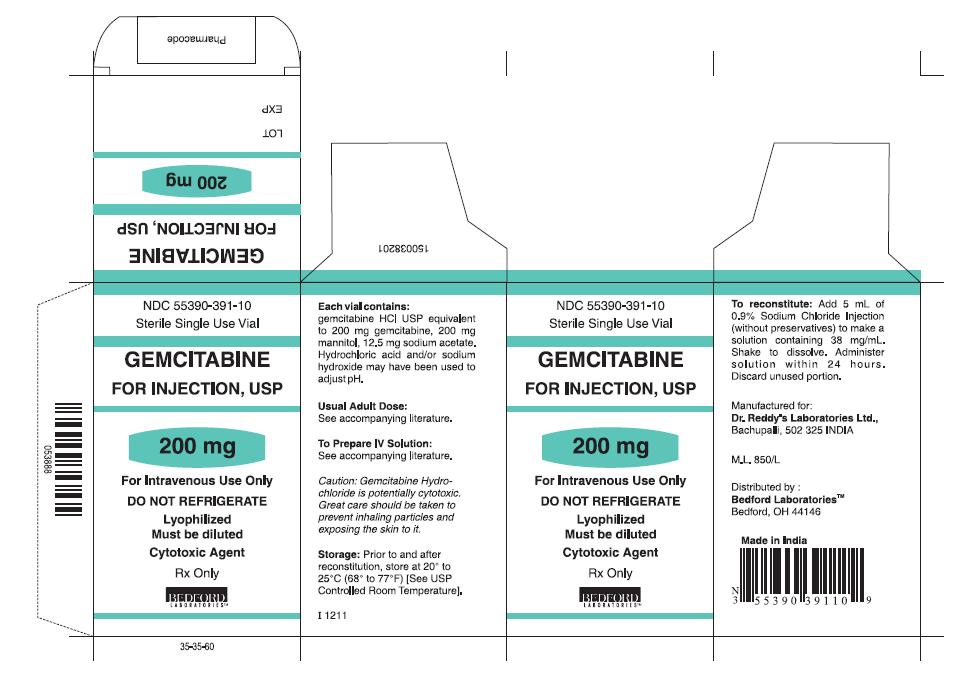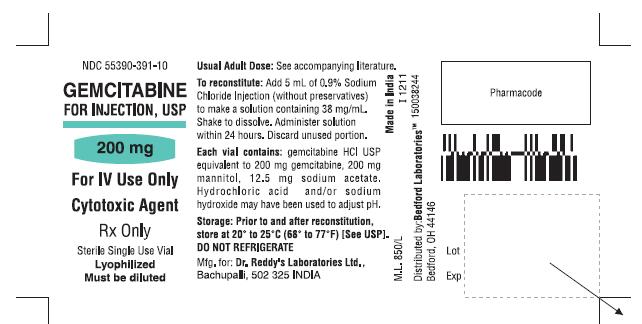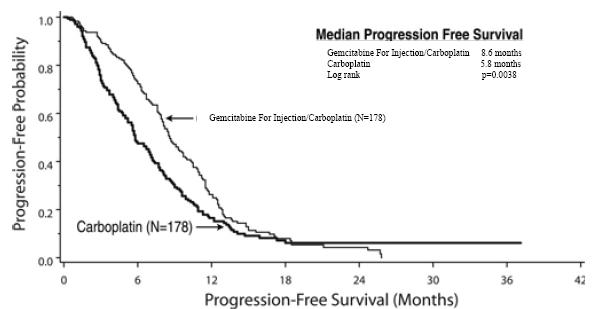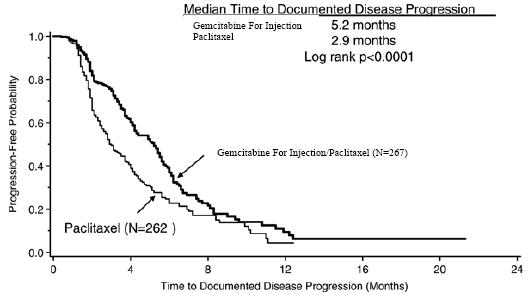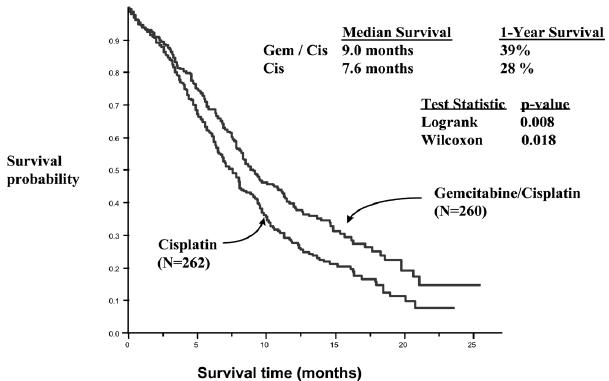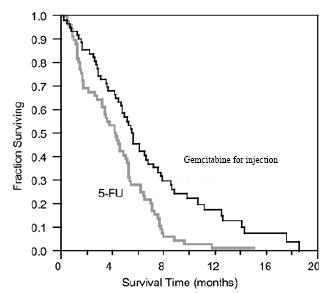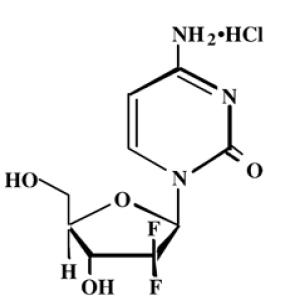 DRUG LABEL: gemcitabine
NDC: 55390-391 | Form: INJECTION, POWDER, LYOPHILIZED, FOR SOLUTION
Manufacturer: Bedford Laboratories
Category: prescription | Type: HUMAN PRESCRIPTION DRUG LABEL
Date: 20140514

ACTIVE INGREDIENTS: gemcitabine hydrochloride 40 mg/1 mL
INACTIVE INGREDIENTS: mannitol; sodium acetate

HIGHLIGHTS OF PRESCRIBING INFORMATION

These highlights do not include all the information needed to use gemcitabine for injection safely and effectively. See full prescribing information for gemcitabine for injection.
Gemcitabine For Injection, Powder, Lyophilized, For Solution For Intravenous Use
Initial U.S. Approval: 1996

RECENT MAJOR CHANGES SECTION

Dosage and Administration:Dose Modifications for Non-Hematologic Adverse Reactions (2.5) 05/2014

Warnings and Precautions:Capillary Leak Syndrome (5.8) 05/2013

Posterior Reversible Encephalopathy Syndrome (5.9) 05/2014

1 INDICATIONS AND USAGE

Gemcitabine for injection is a nucleoside metabolic inhibitor indicated:

- in combination with carboplatin, for the treatment of advanced ovarian cancer that has relapsed at least 6 months after completion of platinum-based therapy (1.1)
- in combination with paclitaxel, for first-line treatment of metastatic breast cancer after failure of prior anthracycline-containing adjuvant chemotherapy, unless anthracyclines were clinically contraindicated (1.2)
- in combination with cisplatin for the treatment of non-small cell lung cancer (1.3)
- as a single agent for the treatment of pancreatic cancer (1.4)

2 DOSAGE AND ADMINISTRATION

Gemcitabine for injection is for intravenous use only.

- Ovarian Cancer: 1000 mg/m^2 over 30 minutes on Days 1 and 8 of each 21-day cycle (2.1)
- Breast Cancer: 1250 mg/m^2 over 30 minutes on Days 1 and 8 of each 21-day cycle (2.2)
- Non-Small Cell Lung Cancer: 1000 mg/m^2 over 30 minutes on Days 1, 8, and 15 of each 28-day cycle or 1250 mg/m^2 over 30 minutes on Days 1 and 8 of each 21-day cycle (2.3)
- Pancreatic Cancer: 1000 mg/m^2 over 30 minutes once weekly for the first 7 weeks, then one week rest, then once weekly for 3 weeks of each 28-day cycle (2.4)

3 DOSAGE FORMS AND STRENGTHS

- 200 mg vial for injection (3)
- 1 g vial for injection (3)

4 CONTRAINDICATIONS

Patients with a known hypersensitivity to Gemcitabine (4)

5 WARNINGS AND PRECAUTIONS

- Schedule-dependent toxicity: Increased toxicity with infusion time greater than 60 minutes or dosing more frequently than once weekly. (5.1)
- Myelosuppression: Monitor for myelosuppression prior to each cycle and reduce or withhold dose for severe myelosuppression. (5.2, 5.7)
- Pulmonary Toxicity and Respiratory Failure: Discontinue gemcitabine for injection immediately for unexplained new or worsening dyspnea or evidence of severe pulmonary toxicity. (5.3)
- Hemolytic-Uremic Syndrome (HUS): Monitor renal function prior to initiation and during therapy. Discontinue gemcitabine for injection for HUS or severe renal impairment. (5.4)
- Hepatic Toxicity: Monitor hepatic function prior to initiation and during therapy. Discontinue gemcitabine for injection for severe hepatic toxicity. (5.5)
- Embryofetal Toxicity: Can cause fetal harm. Advise women of potential risk to the fetus. (5.6, 8.1)
- Exacerbation of Radiation Therapy Toxicity: May cause severe and life-threatening toxicity when administered during or within 7 days of radiation therapy. (5.7)
- Capillary Leak Syndrome: Discontinue gemcitabine for injection. (5.8)
- Posterior reversible encephalopathy syndrome (PRES): Discontinue gemcitabine for injection. (5.9)

6 ADVERSE REACTIONS

The most common adverse reactions for the single agent (≥20%) are nausea/vomiting, anemia, hepatic transaminitis, neutropenia, increased alkaline phosphatase, proteinuria, fever, hematuria, rash, thrombocytopenia, dyspnea, and peripheral edema (6.1)

To report SUSPECTED ADVERSE REACTIONS, contact Dr. Reddy’s Laboratories Inc., at 1-888-375-3784 or FDA at 1-800-FDA-1088 or www.fda.gov/medwatch.

FULL PRESCRIBING INFORMATION

1 INDICATIONS AND USAGE

1.1 Ovarian Cancer

Gemcitabine for injection in combination with carboplatin is indicated for the treatment of patients with advanced ovarian cancer that has relapsed at least 6 months after completion of platinum-based therapy.

1.2 Breast Cancer

Gemcitabine for injection in combination with paclitaxel is indicated for the first-line treatment of patients with metastatic breast cancer after failure of prior anthracycline-containing adjuvant chemotherapy, unless anthracyclines were clinically contraindicated.

1.3 Non-Small Cell Lung Cancer

Gemcitabine for injection is indicated in combination with cisplatin for the first-line treatment of patients with inoperable, locally advanced (Stage IIIA or IIIB), or metastatic (Stage IV) non-small cell lung cancer.

1.4 Pancreatic Cancer

Gemcitabine for injection is indicated as first-line treatment for patients with locally advanced (nonresectable Stage II or Stage III) or metastatic (Stage IV) adenocarcinoma of the pancreas. Gemcitabine for injection is indicated for patients previously treated with 5-FU.

2 DOSAGE AND ADMINISTRATION

Gemcitabine for injection is for intravenous use only. Gemcitabine for injection may be administered on an outpatient basis.

2.1 Ovarian Cancer

Recommended Dose and Schedule

The recommended dose of gemcitabine for injection is 1000 mg/m^2 as an intravenous infusion over 30 minutes on Days 1 and 8 of each 21-day cycle, in combination with carboplatin AUC 4 intravenously after gemcitabine for injection administration on Day 1 of each 21-day cycle. Refer to carboplatin prescribing information for additional information.

Dose Modifications

Recommended gemcitabine for injection dose modifications for myelosuppression are described Table 1 and Table 2 [see Warnings and Precautions (5.2)]. Refer to Dosage and Administration (2.5) for recommendations for non-hematologic adverse reactions.

Table 1: Dosage Reduction Guidelines for Gemcitabine For Injection for Myelosuppression on Day of Treatment in Ovarian Cancer

Treatment Day | Absolute granulocyte count (x 10^6/L) |  | Platelet count (x 10^6/L) | % of full dose
Day 1 | ≥1500 | and | ≥100,000 | 100%
 | <1500 | or | <100,000 | Delay Treatment Cycle
Day 8 | ≥1500 | and | ≥100,000 | 100
 | 1000 to 1499 | or | 75,000 to 99,999 | 50
 | <1000 | or | <75,000 | Hold

Table 2: Gemcitabine For Injection Dose Modification for Myelosuppression in Previous Cycle In Ovarian Cancer

Occurrence | Myelosuppression During Treatment Cycle | Dose Modification
Initial Occurrence | Absolute granulocyte count less than 500 x 10^6/L for more than 5 days Absolute granulocyte count less than 100 x 10^6/L for more than 3 days Febrile neutropenia Platelets less than 25,000x10^6/L Cycle delay of more than one week due to toxicity | Permanently reduce gemcitabine for injection to 800 mg/m^2 on Days 1 and 8
Subsequent Occurrence | If any of the above toxicities occur after the initial dose reduction | Permanently reduce gemcitabine for injection dose to 800 mg/m^2on Day 1 only

2.2 Breast Cancer

Recommended Dose and Schedule

The recommended dose of gemcitabine for injection is 1250 mg/m^2 intravenously over 30 minutes on Days 1 and 8 of each 21-day cycle that includes paclitaxel. Paclitaxel should be administered at 175 mg/m^2 on Day 1 as a 3 hour intravenous infusion before gemcitabine for injection administration.

Dose Modifications Recommended dose modifications for gemcitabine for injection for myelosuppression are described in Table 3 [see Warnings and Precautions (5.2)]. Refer to Dosage and Administration (2.5) for recommendations for non-hematologic adverse reactions.

Table 3: Recommended Dose Reductions for Gemcitabine For Injection for Myelosuppression on Day of Treatment in Breast Cancer

Treatment Day | Absolute granulocyte count (x 10^6/L) |  | Platelet count(x 10^6/L) | % of full dose
Day 1 | ≥1500 | and | ≥ 100,000 | 100%
 | less than1500 | or | less than 100,000 | Hold
Day 8 | ≥ 1200 | and | > 75,000 | 100%
 | 1000 to 1199 | or | 50,000 to 75,000 | 75%
 | 700 to 999 | and | ≥ 50,000 | 50%
 | < 700 | or | < 50,000 | Hold

2.3 Non-Small Cell Lung Cancer

Recommended Dose and Schedule

Every 4-week schedule The recommended dose of gemcitabine for injection is 1000 mg/m^2 intravenously over 30 minutes on Days 1, 8, and 15 in combination with cisplatin therapy. Administer cisplatin intravenously at 100 mg/m^2 on Day 1 after the infusion of gemcitabine for injection.

Every 3-week schedule

The recommended dose of gemcitabine for injection is 1250 mg/m^2 intravenously over 30 minutes on Days 1 and 8 in combination with cisplatin therapy. Administer cisplatin intravenously at 100 mg/m^2 on Day 1 after the infusion of gemcitabine for injection.

Dose Modifications

Recommended dose modifications for gemcitabine for injection myelosuppression are described in Table 4 [see Warnings and Precautions (5.2)]. Refer to Dosage and Administration (2.5) for gemcitabine for injection recommendations for non-hematologic adverse reactions.

2.4 Pancreatic Cancer

Recommended Dose and Schedule

The recommended dose of gemcitabine for injection is 1000 mg/m^2 over 30 minutes intravenously. The recommended treatment schedule

• Weeks 1 to 8: weekly dosing for the first 7 weeks followed by one week rest.

• After week 8: weekly dosing on Days 1, 8, and 15 of 28-day cycles.

Dose Modifications

Recommended dose modifications for gemcitabine for injection for myelosuppression are described in Table 4 [see Warnings and Precautions (5.2)]. Refer to Dosage and Administration (2.5) for recommendations for non-hematologic adverse reactions.

Patients receiving gemcitabine for injection should be monitored prior to each dose with a complete blood count (CBC), including differential and platelet count. If marrow suppression is detected, therapy should be modified or suspended according to the guidelines in Table 4.

Table 4: Recommended Dose Reductions for Gemcitabine For Injection for Myelosuppression in Pancreatic Cancer and Non-Small Cell Lung Cancer

Absolute granulocyte count (x 10^6/L) |  | Platelet count(x 10^6/L) | % of full dose
≥1000 | And | ≥100,000 | 100
500 to 999 | Or | 50,000 to 99,999 | 75
<500 | Or | <50,000 | Hold

2.5 Dose Modifications for Non-Hematologic Adverse Reactions

Permanently discontinue gemcitabine for injection for any of the following

- Unexplained dyspnea or other evidence of severe pulmonary toxicity
- Severe hepatic toxicity
- Hemolytic-Uremic Syndrome
- Capillary Leak Syndrome
- Posterior reversible encephalopathy syndrome

Withhold gemcitabine for injection or reduce dose by 50% for other severe (Grade 3 or 4) non-hematological toxicity until resolved. No dose modifications are recommended for alopecia, nausea, or vomiting.

2.6 Preparation and Administration Precautions

Exercise caution and wear gloves when preparing gemcitabine for injection solutions. Immediately wash the skin thoroughly or rinse the mucosa with copious amounts of water if gemcitabine for injection contacts the skin or mucus membranes. Death has occurred in animal studies due to dermal absorption. For further guidance on handling gemcitabine for injection go to “OSHA Hazardous Drugs” (refer to antineoplastic weblinks including OSHA Technical Manual) at OSHA. http://www.osha.gov/SLTC/hazardousdrugs/index.html

2.7 Preparation for Intravenous Infusion Administration

Reconstitute the vials with 0.9% Sodium Chloride Injection without preservatives. Add 5 mL to the 200 mg vial or 25 mL to the 1 g vial. These dilutions each yield a gemcitabine for injection concentration of 38 mg/mL. Complete withdrawal of the vial contents will provide 200 mg or 1 g of gemcitabine for injection. Prior to administration the appropriate amount of drug must be diluted with 0.9% Sodium Chloride Injection. Final concentrations may be as low as 0.1 mg/mL.

Reconstituted gemcitabine for injection is a clear, colorless to light straw-colored solution. Inspect visually prior to administration and discard for particulate matter or discoloration. Gemcitabine for injection solutions are stable for 24 hours at controlled room temperature of 20° to 25°C (68° to 77°F). Do not refrigerate as crystallization can occur.

No incompatibilities have been observed with infusion bottles or polyvinyl chloride bags and administration sets.

3 DOSAGE FORMS AND STRENGTHS

Gemcitabine for injection, USP 200 mg is a white, lyophilized powder available in sterile single-use vials containing 200 mg gemcitabine.

Gemcitabine for injection, USP 1 gm is a white, lyophilized powder available in sterile single-use vials containing 1 g gemcitabine.

4 CONTRAINDICATIONS

Gemcitabine for injection is contraindicated in patients with a known hypersensitivity to gemcitabine.

5 WARNINGS AND PRECAUTIONS

Patients receiving therapy with gemcitabine for injection should be monitored closely by a physician experienced in the use of cancer chemotherapeutic agents.

5.1 Schedule-dependent Toxicity

In clinical trials evaluating the maximum tolerated dose of gemcitabine for injection, prolongation of the infusion time beyond 60 minutes or more frequent than weekly dosing resulted in an increased incidence of clinically significant hypotension, severe flu-like symptoms, myelosuppression, and asthenia. The half-life of gemcitabine for injection is influenced by the length of the infusion [see Clinical Pharmacology (12.3)].

5.2 Myelosuppression

Myelosuppression manifested by neutropenia, thrombocytopenia, and anemia occurs with gemcitabine for injection as a single agent and the risks are increased when gemcitabine for injection is combined with other cytotoxic drugs. In clinical trials, Grade 3-4 neutropenia, anemia, and thrombocytopenia occurred in 25%, 8%, and 5%, respectively of patients receiving single-agent. The frequencies of Grade 3-4 neutropenia, anemia, and thrombocytopenia varied from 48% to 71%, 8 to 28%, and 5 to 55%, respectively, in patients receiving gemcitabine for injection in combination with another drug.

5.3 Pulmonary Toxicity and Respiratory Failure

Pulmonary toxicity, including interstitial pneumonitis, pulmonary fibrosis, pulmonary edema, and adult respiratory distress syndrome (ARDS), has been reported. In some cases, these pulmonary events can lead to fatal respiratory failure despite discontinuation of therapy. The onset of pulmonary symptoms may occur up to 2 weeks after the last dose of gemcitabine for injection. Discontinue gemcitabine for injection in patients who develop unexplained dyspnea, with or without bronchospasm, or have any evidence of pulmonary toxicity [see Adverse Reactions (6.1 and 6.2)].

5.4 Hemolytic Uremic Syndrome

Hemolytic Uremic Syndrome to include fatalities from renal failure or the requirement for dialysis can occur in patients treated with gemcitabine for injection. In clinical trials, HUS was reported in 6 of 2429 patients (0.25%). Most fatal cases of renal failure were due to HUS [see Adverse Reactions (6.1 and 6.2)]. Assess renal function prior to initiation of gemcitabine for injection and periodically during treatment. Consider the diagnosis of HUS in patients who develops anemia with evidence of microangiopathic hemolysis, elevation of bilirubin or LDH, or reticulocytosis; severe thrombocytopenia; or evidence of renal failure (elevation of serum creatinine or BUN) [see Dosage and Administration (2.5) and Use In Specific Populations (8.6)]. Permanently discontinue gemcitabine for injection in patients with HUS or severe renal impairment. Renal failure may not be reversible even with discontinuation of therapy. Renal failure may not be reversible even with discontinuation of therapy.

5.5 Hepatic Toxicity

Drug-induced liver injury, including liver failure and death, has been reported in patients receiving gemcitabine for injection alone or in combination with other potentially hepatotoxic drugs [see Adverse Reactions (6.1 and 6.2)]. Administration of gemcitabine for injection in patients with concurrent liver metastases or a pre-existing medical history or hepatitis, alcoholism, or liver cirrhosis can lead to exacerbation of the underlying hepatic insufficiency [see Use in Specific Populations (8.7)]. Assess hepatic function prior to initiation of gemcitabine for injection and periodically during treatment. Discontinue gemcitabine for injection in patients that develop severe liver injury.

5.6 Embryofetal Toxicity

Gemcitabine for injection can cause fetal harm when administered to a pregnant woman, based on its mechanism of action. Gemcitabine was teratogenic, embryotoxic, and fetotoxic in mice and rabbits. If this drug is used during pregnancy, or if a woman becomes pregnant while taking gemcitabine for injection, the patient should be apprised of the potential hazard to a fetus. [see Use In Specific Populations (8.1)]

5.7 Exacerbation of Radiation Therapy Toxicity

Gemcitabine for injection is not indicated for use in combination with radiation therapy.

Concurrent (given together or ≤7 days apart) — Life-threatening mucositis, especially esophagitis and pneumonitis occurred in a trial in which gemcitabine for injection was administered at a dose of 1000 mg/m^2 to patients with non-small cell lung cancer for up to 6 consecutive weeks concurrently with thoracic radiation.

Non-concurrent (given >7 days apart) — Excessive toxicity has not been observed when gemcitabine for injection is administered more than 7 days before or after radiation. Radiation recall has been reported in patients who receive gemcitabine for injection after prior radiation.

5.8 Capillary Leak Syndrome

Capillary leak syndrome (CLS) with severe consequences has been reported in patients receiving gemcitabine for injection as a single agent or in combination with other chemotherapeutic agents. Discontinue gemcitabine for injection if CLS develops during therapy.

5.9 Posterior Reversible Encephalopathy Syndrome

Posterior reversible encephalopathy syndrome (PRES) has been reported in patients receiving gemcitabine for injection as a single agent or in combination with other chemotherapeutic agents. PRES can present with headache, seizure, lethargy, hypertension, confusion, blindness, and other visual and neurologic disturbances. Confirm the diagnosis of PRES with magnetic resonance imaging (MRI) and discontinue gemcitabine for injection if PRES develops during therapy.

6 ADVERSE REACTIONS

The following serious adverse reactions are discussed in greater detail in another section of the label

- Schedule-Dependent Toxicity [see Warnings and Precautions (5.1) ]
- Myelosuppression [see Warnings and Precautions (5.2)]
- Pulmonary Toxicity and Respiratory Failure [see Warnings and Precautions (5.3)]
- Hemolytic Uremic Syndrome [see Warnings and Precautions (5.4)]
- Hepatic Toxicity [see Warnings and Precautions (5.5)]
- Embryo-fetal Toxicity [ see Warnings and Precautions (5.6), Use in Specific Populations (8.1), and Nonclinical Toxicology (13.1)].
- Posterior Reversible Encephalopathy Syndrome [see Warnings and Precautions (5.9)]

6.1 Clinical Trials Experience

Because clinical trials are conducted under widely varying conditions, adverse reaction rates observed in the clinical trials of a drug cannot be directly compared to rates in the clinical trials of another drug and may not reflect the rates observed in clinical practice.

Single-Agent Use:

The data described below reflect exposure to gemcitabine for injection as a single agent administered at doses between 800 mg/m^2 to 1250 mg/m^2 over 30 minutes intravenously, once weekly, in 979 patients with a variety of malignancies. The most common (≥20%) adverse reactions of single-agent gemcitabine for injection are nausea/vomiting, anemia, increased ALT, increased AST, neutropenia, increased alkaline phosphatase, proteinuria, fever, hematuria, rash, thrombocytopenia, dyspnea, and edema. The most common (≥5%) Grade 3 or 4 adverse reactions were neutropenia, nausea/vomiting; increased ALT, increase alkaline phosphatase, anemia, increased AST, and thrombocytopenia. Approximately 10% of the 979 patients discontinued gemcitabine for injection due to adverse reactions. Adverse reactions resulting in discontinuation of gemcitabine for injection in 2% of 979 patients were cardiovascular adverse events (myocardial infarction, cerebrovascular accident, arrhythmia, and hypertension) and adverse reactions resulting in discontinuation of gemcitabine for injection in less than 1% of the 979 patients were anemia, thrombocytopenia, hepatic dysfunction, renal dysfunction, nausea/vomiting, fever, rash, dyspnea, hemorrhage, infection, stomatitis, somnolence, flu-like syndrome, and edema.

Table 5 presents the incidence of adverse reactions reported in 979 patients with various malignancies receiving single-agent gemcitabine for injection across 5 clinical trials. Table 5 includes all clinical adverse reactions, reported in at least 10% of patients. A listing of clinically significant adverse reactions is provided following the table.

Table 5: Selected Per-Patient Incidence of Adverse Events in Patients Receiving Single-Agent Gemcitabine For Injectiona

 | All Patients b
 | All Grades | Grade 3 | Grade 4
Laboratoryc
Hematologic
Anemia | 68 | 7 | 1
Neutropenia | 63 | 19 | 6
Thrombocytopenia | 24 | 4 | 1
Hepatic
Increased ALT | 68 | 8 | 2
Increased AST | 67 | 6 | 2
Increased Alkaline Phosphatase | 55 | 7 | 2
Hyperbilirubinemia | 13 | 2 | <1
Renal
Proteinuria | 45 | <1 | 0
Hematuria | 35 | <1 | 0
Increased BUN | 16 | 0 | 0
Increased Creatinine | 8 | <1 | 0
Non– laboratoryd
Nausea and Vomiting | 69 | 13 | 1
Fever | 41 | 2 | 0
Rash | 30 | <1 | 0
Dyspnea | 23 | 3 | <1
Diarrhea | 19 | 1 | 0
Hemorrhage | 17 | <1 | <1
Infection | 16 | 1 | <1
Alopecia | 15 | <1 | 0
Stomatitis | 11 | <1 | 0
Somnolence | 11 | <1 | <1
Paresthesias | 10 | <1 | 0

a Grade based on criteria from the World Health Organization (WHO).

b N=699-974; all patients with laboratory or non-laboratory data.

c Regardless of causality.

d For approximately 60% of patients, non-laboratory adverse events were graded only if assessed to be possibly drug-related.

- Transfusion requirements — Red blood cell transfusions (19%); platelet transfusions (<1%)
- Fever — Fever occurred in the absence of clinical infection and frequently in combination with other flu-like symptoms.
- Pulmonary — Dyspnea unrelated to underlying disease and sometimes accompanied by bronchospasm.
- Edema — Edema (13%), peripheral edema (20%), and generalized edema (<1%); <1% of patients. discontinued gemcitabine for injection due to edema.
- Flu-like Symptoms — Characterized by fever, asthenia, anorexia, headache, cough, chills, myalgia, asthenia insomnia, rhinitis, sweating, and/or malaise (19%); <1% of patients discontinued gemcitabine for injection due to flu-like symptoms
- Infection — Sepsis (<1%)
- Extravasation — Injection-site reactions (4%)
- Allergic — Bronchospasm (<2%); anaphylactoid reactions [see Contraindications (4)].

Non-Small Cell Lung Cancer:

Table 6 presents the incidence of selected adverse reactions, occurring in ≥10% of gemcitabine for injection-treated patients and at a higher incidence in the gemcitabine for injection plus cisplatin arm, reported in a randomized trial of gemcitabine for injection plus cisplatin (n=262) administered in 28-day cycles as compared to cisplatin alone (n=260) in patients receiving first-line treatment for locally advanced or metastatic non-small cell lung cancer (NSCLC) [see Clinical Studies (14.3)].

Patients randomized to gemcitabine for injection plus cisplatin received a median of 4 cycles of treatment and those randomized to cisplatin received a median of 2 cycles of treatment. In this trial, the requirement for dose adjustments (>90% versus 16%), discontinuation of treatment for adverse reactions (15% versus 8%), and the proportion of patients hospitalized (36% versus 23%) were all higher for patients receiving gemcitabine for injection plus cisplatin arm compared to those receiving cisplatin alone. The incidence of febrile neutropenia (9/262 versus 2/260), sepsis (4% versus 1%), Grade 3 cardiac dysrhythmias (3% versus <1%) were all higher in the gemcitabine for injection plus cisplatin arm compared to the cisplatin alone arm. The two-drug combination was more myelosuppressive with 4 (1.5%) possibly treatment-related deaths, including 3 resulting from myelosuppression with infection and one case of renal failure associated with pancytopenia and infection. No deaths due to treatment were reported on the cisplatin arm.

Table 6: Per-Patient Incidence of Selected Adverse Reactions from Randomized Trial of Gemcitabine For Injection plus Cisplatin versus Single-Agent Cisplatin in Patients with NSCLC Occurring at Higher Incidence in Gemcitabine For Injection-Treated Patients [Between Arm Difference of ≥5% (All Grades) or ≥2% (Grades 3 - 4)] a

 | Gemcitabine For Injection plus Cisplatin b |  |  | Cisplatin c
 | All Grades | Grade 3 | Grade 4 | All Grades | Grade 3 | Grade 4
Laboratoryd
Hematologic
Anemia | 89 | 22 | 3 | 67 | 6 | 1
RBC Transfusion e | 39 |  |  | 13
Neutropenia | 79 | 22 | 35 | 20 | 3 | 1
Thrombocytopenia | 85 | 25 | 25 | 13 | 3 | 1
Platelet Transfusion e | 21 |  |  | <1
Lymphopenia | 75 | 25 | 18 | 51 | 12 | 5
Hepatic
Increased Transaminases | 22 | 2 | 1 | 10 | 1 | 0
Increased Alkaline Phosphatase | 19 | 1 | 0 | 13 | 0 | 0
Renal
Proteinuria | 23 | 0 | 0 | 18 | 0 | 0
Hematuria | 15 | 0 | 0 | 13 | 0 | 0
Elevated creatinine | 38 | 4 | <1 | 31 | 2 | <1
Other Laboratory
Hyperglycemia | 30 | 4 | 0 | 23 | 3 | 0
Hypomagnesemia | 30 | 4 | 3 | 17 | 2 | 0
Hypocalcemia | 18 | 2 | 0 | 7 | 0 | <1
Non-laboratoryf
Nausea | 93 | 25 | 2 | 87 | 20 | <1
Vomiting | 78 | 11 | 12 | 71 | 10 | 9
Alopecia | 53 | 1 | 0 | 33 | 0 | 0
Neuro Motor | 35 | 12 | 0 | 15 | 3 | 0
Diarrhea | 24 | 2 | 2 | 13 | 0 | 0
Neuro Sensory | 23 | 1 | 0 | 18 | 1 | 0
Infection | 18 | 3 | 2 | 12 | 1 | 0
Fever | 16 | 0 | 0 | 5 | 0 | 0
Neuro Cortical | 16 | 3 | 1 | 9 | 1 | 0
Neuro Mood | 16 | 1 | 0 | 10 | 1 | 0
Local | 15 | 0 | 0 | 6 | 0 | 0
Neuro Headache | 14 | 0 | 0 | 7 | 0 | 0
Stomatitis | 14 | 1 | 0 | 5 | 0 | 0
Hemorrhage | 14 | 1 | 0 | 4 | 0 | 0
Hypotension | 12 | 1 | 0 | 7 | 1 | 0
Rash | 11 | 0 | 0 | 3 | 0 | 0

a National Cancer Institute Common Toxicity Criteria (CTC) for severity grading.

b N=217–253; all gemcitabine for injection plus cisplatin patients with laboratory or non–laboratory data gemcitabine for injection at 1000 mg/m^2 on Days 1, 8, and 15 and cisplatin at 100 mg/m^2 on Day 1 every 28 days.

c N=213–248; all cisplatin patients with laboratory or non–laboratory data. Cisplatin at 100 mg/m^2 on Day 1 every 28 days.

d Regardless of causality.

e Percent of patients receiving transfusions. Percent transfusions are not CTC–graded events.

f Non–laboratory events were graded only if assessed to be possibly drug–related.

Table 7 presents the incidence of selected adverse reactions, occurring in ≥10% of gemcitabine for injection-treated patients and at a higher incidence in the gemcitabine for injection plus cisplatin arm, reported in a randomized trial of gemcitabine for injection plus cisplatin (n=69) administered in 21-day cycles as compared to etoposide plus cisplatin alone (n=66) in patients receiving first-line treatment for locally advanced or metastatic non-small cell lung cancer (NSCLC) [see Clinical Studies (14.3)]. A listing of clinically significant adverse reactions is provided following the table.

Patients in the gemcitabine for injection cisplatin (GC) arm received a median of 5 cycles and those in the etoposide/cisplatin (EC) arm received a median of 4 cycles. The majority of patients receiving more than one cycle of treatment required dose adjustments; 81% in the (GC) arm and 68% in the (EC) arm. The incidence of hospitalizations for treatment-related adverse events was 22% (GC) and 27% in the (EC) arm. The proportion of discontinuation of treatment for treatment-related adverse reactions was higher for patients in the (GC) arm (14% versus 8%). The proportion of patients hospitalized for febrile neutropenia was lower in the (GC) arm (7% versus 12%). There was one death attributed to treatment, a patient with febrile neutropenia and renal failure, which occurred in the gemcitabine for injection /cisplatin arm.

Table 7: Per-Patient Incidence of Selected Adverse Reactions in Randomized Trial of Gemcitabine For Injection plus Cisplatin versus Etoposide plus Cisplatin in Patients with NSCLCa

 | Gemcitabine For Injection plus Cisplatinb |  |  | Etoposide plus Cisplatinc
 | All Grades | Grade 3 | Grade 4 | All Grades | Grade 3 | Grade 4
Laboratoryd
Hematologic
Anemia | 88 | 22 | 0 | 77 | 13 | 2
RBC Transfusionse | 29 | - | - | 21 | - | -
Neutropenia | 88 | 36 | 28 | 87 | 20 | 56
Thrombocytopenia | 81 | 39 | 16 | 45 | 8 | 5
Platelet Transfusionse | 3 | - | - | 8 | - | -
Hepatic
Increased ALT | 6 | 0 | 0 | 12 | 0 | 0
Increased AST | 3 | 0 | 0 | 11 | 0 | 0
Increased Alkaline | 16 | 0 | 0 | 11 | 0 | 0
Phosphatase
Bilirubin | 0 | 0 | 0 | 0 | 0 | 0
Renal
Proteinuria | 12 | 0 | 0 | 5 | 0 | 0
Hematuria | 22 | 0 | 0 | 10 | 0 | 0
BUN | 6 | 0 | 0 | 4 | 0 | 0
Creatinine | 2 | 0 | 0 | 2 | 0 | 0
Non– laboratoryf,g
Nausea and Vomiting | 96 | 35 | 4 | 86 | 19 | 7
Fever | 6 | 0 | 0 | 3 | 0 | 0
Rash | 10 | 0 | 0 | 3 | 0 | 0
Dyspnea | 1 | 0 | 1 | 3 | 0 | 0
Diarrhea | 14 | 1 | 1 | 13 | 0 | 2
Hemorrhage | 9 | 0 | 3 | 3 | 0 | 3
Infection | 28 | 3 | 1 | 21 | 8 | 0
Alopecia | 77 | 13 | 0 | 92 | 51 | 0
Stomatitis | 20 | 4 | 0 | 18 | 2 | 0
Somnolence | 3 | 0 | 0 | 3 | 2 | 0
Paresthesias | 38 | 0 | 0 | 16 | 2 | 0

a Grade based on criteria from the World Health Organization (WHO).

b N=67–69; all gemcitabine for injection plus cisplatin patients with laboratory or non–laboratory data. Gemcitabine for injection at 1250 mg/m^2 on Days 1 and 8 and cisplatin at 100 mg/m^2 on Day 1 every 21 days.

c N=57–63; all cisplatin plus etoposide patients with laboratory or non–laboratory data. Cisplatin at 100 mg/m^2 on Day 1 and intravenous etoposide at 100 mg/m^2 on Days 1, 2, and 3 every 21 days.

dRegardless of causality.

e WHO grading scale not applicable to proportion of patients with transfusions

fNon–laboratory events were graded only if assessed to be possibly drug–related.

g Pain data were not collected.

- Flu-like syndrome: 3% in the gemcitabine for injection/cisplatin arm versus none in the etoposide/cisplatin arm.
- Edema: 12% in the gemcitabine for injection/cisplatin arm versus 2% in the etoposide/cisplaarm.tin

Breast CancerTable 8 presents the incidence of selected adverse reactions, occurring in ≥10% of gemcitabine for injection-treated patients and at a higher incidence in the gemcitabine for injection plus paclitaxel arm, reported in a randomized trial of gemcitabine for injection plus paclitaxel (n=262) compared to paclitaxel alone (n=259) for the first-line treatment of metastatic breast cancer (MBC) in women who received anthracycline-containing chemotherapy in the adjuvant/neo-adjuvant setting or for whom anthracyclines were contraindicated. [see Clinical Studies (14.2)].

The requirement for dose reduction of paclitaxel were higher for patients in the gemcitabine for injection/paclitaxel arm (5% versus 2%). The number of paclitaxel doses omitted (<1%), the proportion of patients discontinuing treatment for treatment-related adverse reactions (7% versus 5%), and the number of treatment-related deaths (1 patient in each arm) were similar between the two arms.

Table 8: Per-Patient Incidence of Selected Adverse Reactions from Comparative Trial of Gemcitabine For Injection plus Paclitaxel versus Single-Agent Paclitaxel in Breast Cancera Occurring at Higher Incidence in Gemcitabine For Injection-Treated Patients [Between Arm Difference of ≥5% (All Grades) or ≥2% (Grades 3 - 4)]

 | Gemcitabine For Injection plus Paclitaxel (N=262) |  |  | Paclitaxel (N=259)
 | All Grades | Grade 3 | Grade 4 | All Grades | Grade 3 | Grade 4
Laboratoryb
Hematologic
Anemia | 69 | 6 | 1 | 51 | 3 | <1
Neutropenia | 69 | 31 | 17 | 31 | 4 | 7
Thrombocytopenia | 26 | 5 | <1 | 7 | <1 | <1
Hepatobiliary
Increased ALT | 18 | 5 | <1 | 6 | <1 | 0
Increased AST | 16 | 2 | 0 | 5 | <1 | 0
Non– laboratoryc
Alopecia | 90 | 14 | 4 | 92 | 19 | 3
Neuropathy– sensory | 64 | 5 | <1 | 58 | 3 | 0
Nausea | 50 | 1 | 0 | 31 | 2 | 0
Fatigue | 40 | 6 | <1 | 28 | 1 | <1
Vomiting | 29 | 2 | 0 | 15 | 2 | 0
Diarrhea | 20 | 3 | 0 | 13 | 2 | 0
Anorexia | 17 | 0 | 0 | 12 | <1 | 0
Neuropathy– motor | 15 | 2 | <1 | 10 | <1 | 0
Stomatitis/ pharyngitis | 13 | 1 | <1 | 8 | <1 | 0
Fever | 13 | <1 | 0 | 3 | 0 | 0
Rash/ desquamation | 11 | <1 | <1 | 5 | 0 | 0

a Severity grade based on National Cancer Institute Common Toxicity Criteria (CTC) Version 2.0

b Regardless of causality.

c Non–laboratory events were graded only if assessed to be possibly drug–relate

The following clinically relevant, Grade 3 or 4 adverse reactions occurred with a higher incidence in the gemcitabine for injection plus paclitaxel arm compared with paclitaxel arm: febrile neutropenia (5% versus 1.2%) and dyspnea (1.9%versus 0)

Ovarian Cancer

Table 9 presents the incidence of selected adverse reactions, occurring in ≥10% of gemcitabine-treated patients and at a higher incidence in the gemcitabine for injection plus carboplatin arm, reported in a randomized trial of gemcitabine for injection plus carboplatin (n=175) compared to carboplatin alone (n=174) for the second-line treatment of ovarian cancer in women with disease that had relapsed more than 6 months following first-line platinum-based chemotherapy. [see Clinical Studies (14.1)]. Additional clinically significant adverse reactions, occurring in less than 10% of patients, are provided following Table 9.

The proportion of patients with dose adjustments for carboplatin (1.8% versus 3.8%), doses of carboplatin omitted (0.2% versus 0), and discontinuing treatment for treatment-related adverse reactions (10.9% versus 9.8%), were similar between arms. Dose adjustment for gemcitabine for injection occurred in 10.4% of patients and gemcitabine for injection dose was omitted in 13.7% of patients in the gemcitabine for injection /carboplatin arm.

Table 9: Per-Patient Incidence of Adverse Reactions in Randomized Trial of Gencitabine For Injection plus Carboplatin versus Carboplatin in Ovarian Cancer Occurring at Higher Incidence in Gemcitabine For Injection-Treated Patients [Between Arm Difference of ≥ 5% (All Grades) or ≥2% (Grades 3-4)]

 | Gemcitabine For Injection plus Carboplatin (N=175) |  |  | Carboplatin (N=174)
 | All Grades | Grade 3 | Grade 4 | All Grades | Grade 3 | Grade 4
Laboratoryb
Hematologic
Neutropenia | 90 | 42 | 29 | 58 | 11 | 1
Anemia | 86 | 22 | 6 | 75 | 9 | 2
Thrombocytopenia | 78 | 30 | 5 | 57 | 10 | 1
RBC Transfusionsc | 38 |  |  | 15
Platelet Transfusionsc | 9 |  |  | 3
Non–laboratoryb
Nausea | 69 | 6 | 0 | 61 | 3 | 0
Alopecia | 49 | 0 | 0 | 17 | 0 | 0
Vomiting | 46 | 6 | 0 | 36 | 2 | <1
Constipation | 42 | 6 | 1 | 37 | 3 | 0
Fatigue | 40 | 3 | <1 | 32 | 5 | 0
Diarrhea | 25 | 3 | 0 | 14 | <1 | 0
Stomatitis/ pharyngitis | 22 | <1 | 0 | 13 | 0 | 0

a Grade based on Common Toxicity Criteria (CTC) Version 2.0.

b Regardless of causality.

c Percent of patients receiving transfusions. Transfusions are not CTC–graded events. Blood transfusions included both packed red blood cells and whole blood.

Hematopoietic growth factors were administered more frequently in the gemcitabine for injection-containing arm: granulocyte growth factors (23.6% and 10.1%) and erythropoietic agents (7.3% and 3.9%).

The following clinically relevant, Grade 3 and 4 adverse reactions occurred more frequently in the gemcitabine for injection plus carboplatin arm: dyspnea (3.4% versus 2.9%), febrile neutropenia (1.1% versus 0), hemorrhagic event (2.3% versus 1.1 %), motor neuropathy (1.1% versus 0.6%), and rash/desquamation (0.6% versus 0).

6.2 Post-Marketing Experience

The following adverse reactions have been identified during post-approval use of gemcitabine for injection. Because these reactions are reported voluntarily from a population of uncertain size, it is not always possible to reliably estimate their frequency or establish a causal relationship to drug exposure.

Cardiovascular — Congestive heart failure, myocardial infarction, Arrhythmias, supraventricular arrhythmias.

Vascular Disorders — Peripheral vasculitis, gangrene, and capillary leak syndrome [see Warnings and Precautions (5.9)]

Skin — Cellulitis, severe skin reactions, including desquamation and bullous skin eruptions

Hepatic — Hepatic failure, hepatic veno-occlusive disease

Pulmonary — Interstitial pneumonitis, pulmonary fibrosis, pulmonary edema, and adult respiratory distress syndrome (ARDS)

Nervous System — Posterior reversible encephalopathy syndrome (PRES) [see Warnings and Precautions (5.9)]

7 DRUG INTERACTIONS

No drug interaction studies have been conducted.

8 USE IN SPECIFIC POPULATIONS

8.1 Pregnancy

Pregnancy Category D. [see Warnings and Precautions (5.6)].

Risk Summary

Gemcitabine for injection can cause fetal harm when administered to a pregnant woman. Based on its mechanism of action, gemcitabine for injection is expected to result in adverse reproductive effects. Gemcitabine was teratogenic, embryotoxic, and fetotoxic in mice and rabbits. If gemcitabine for injection is used during pregnancy, or if the patient becomes pregnant while taking gemcitabine for injection, the patient should be apprised of the potential hazard to a fetus.

Animal Data

Gemcitabine is embryotoxic causing fetal malformations (cleft palate, incomplete ossification) at doses of 1.5 mg/kg/day in mice (approximately 0.005 times the recommended human dose on a mg/m^2 basis). Gemcitabine is fetotoxic causing fetal malformations (fused pulmonary artery, absence of gall bladder) at doses of 0.1 mg/kg/day in rabbits (about 0.002 times the recommended human dose on a mg/m^2 basis). Embryotoxicity was characterized by decreased fetal viability, reduced live litter sizes, and developmental delays. [see Warnings and Precautions (5.6)]

8.3 Nursing Mothers

It is not known whether this drug is excreted in human milk. Because many drugs are excreted in human milk and because of the potential for serious adverse reactions in nursing infants from Gemcitabine for injection, a decision should be made whether to discontinue nursing or to discontinue the drug, taking into account the importance of the drug to the mother.

8.4 Pediatric Use

The safety and effectiveness of gemcitabine for injection have not been established in pediatric patients. The safety and pharmacokinetics of gemcitabine were evaluated in a trial in pediatric patients with refractory leukemia. The maximum tolerated dose was 10 mg/m^2/min for 360 minutes three times weekly followed by a one-week rest period. The safety and activity of gemcitabine for injection were evaluated in a trial of pediatric patients with relapsed acute lymphoblastic leukemia (22 patients) and acute myelogenous leukemia (10 patients) at a dose of 10 mg/m^2/min administered over 360 minutes three times weekly followed by a one-week rest period. Toxicities observed included bone marrow suppression, febrile neutropenia, elevation of serum transaminases, nausea, and rash/desquamation. No meaningful clinical activity was observed in this trial.

8.5 Geriatric Use

In clinical studies of gemcitabine for injection, enrolling 979 patients with various cancers who received gemcitabine for injection as a single agent, no overall differences in safety were observed between patients aged 65 and older and younger patients, with the exception of a higher rate of Grade 3-4 thrombocytopenia in older patients as compared to younger patients. In a randomized trial in women with ovarian cancer, 175 women received gemcitabine for injection plus carboplatin, of which 29% were age 65 years or older. Similar effectiveness was observed between older and younger women. There was significantly higher Grade 3/4 neutropenia in women 65 years of age or older.

Gemcitabine for injection clearance is affected by age, however there are no recommended dose adjustments based on patients’ age [see Clinical Pharmacology (12.3)].

8.6 Renal Impairment

No clinical studies have been conducted with gemcitabine in patients with decreased renal function.

8.7 Hepatic Impairment

No clinical studies have been conducted with gemcitabine in patients with decreased hepatic function.

8.8 Gender

Gemcitabine for injection clearance is affected by gender. [see Clinical Pharmacology (12.3)]. In single-agent studies of gemcitabine for injection women, especially older women, were more likely not to proceed to a subsequent cycle and to experience Grade 3/4 neutropenia and thrombocytopenia.

10 OVERDOSAGE

Myelosuppression, paresthesias, and severe rash were the principal toxicities seen when a single dose as high as 5700 mg/m^2 was administered by intravenous infusion over 30 minutes every 2 weeks to several patients in a dose-escalation study.

11 DESCRIPTION

Gemcitabine for injection, USP is a nucleoside metabolic inhibitor that exhibits antitumor activity. Gemcitabine HCl USP is 2´-deoxy-2´,2´-difluorocytidine monohydrochloride (β-isomer).

The structural formula is as follows:

The molecular formula for gemcitabine HCl is C9H11F2N3O4 • HCl. It has a molecular weight of 299.66.

Gemcitabine HCl USP is a white to off-white solid. It is soluble in water, slightly soluble in methanol, and practically insoluble in ethanol and polar organic solvents.

Gemcitabine for Injection is supplied in a sterile form for intravenous use only. Vials of gemcitabine for injection, USP contain either 200 mg or 1 g of gemcitabine HCl USP (expressed as free base) formulated with mannitol (200 mg or 1 g, respectively) and sodium acetate trihydrate (20.73 mg or 103.5 mg), or sodium acetate (12.5 mg or 62.5 mg), respectively as a sterile lyophilized powder. Hydrochloric acid and/or sodium hydroxide may have been added for pH adjustment.

12 CLINICAL PHARMACOLOGY

12.1 Mechanism of Action

Gemcitabine kills cells undergoing DNA synthesis and blocks the progression of cells through the G1/S-phase boundary. Gemcitabine is metabolized by nucleoside kinases to diphosphate (dFdCDP) and triphosphate (dFdCTP) nucleosides. Gemcitabine diphosphate inhibits ribonucleotide reductase, an enzyme responsible for catalyzing the reactions that generate deoxynucleoside triphosphates for DNA synthesis, resulting in reductions in deoxynucleotide concentrations, including dCTP. Gemcitabine triphosphate competes with dCTP for incorporation into DNA. The reduction in the intracellular concentration of dCTP by the action of the diphosphate enhances the incorporation of gemcitabine triphosphate into DNA (self-potentiation). After the gemcitabine nucleotide is incorporated into DNA, only one additional nucleotide is added to the growing DNA strands, which eventually results in the initiation of apoptotic cell death.

12.3 Pharmacokinetics

Absorption and Distribution

The pharmacokinetics of gemcitabine were examined in 353 patients, with various solid tumors. Pharmacokinetic parameters were derived using data from patients treated for varying durations of therapy given weekly with periodic rest weeks and using both short infusions (<70 minutes) and long infusions (70 to 285 minutes). The total gemcitabine for injection dose varied from 500 to 3600 mg/m^2.

The volume of distribution was increased with infusion length. Volume of distribution of gemcitabine was 50 L/m^2 following infusions lasting <70 minutes. For long infusions, the volume of distribution rose to 370 L/m^2.

Metabolism

Gemcitabine disposition was studied in 5 patients who received a single 1000 mg/m^2/30 minute infusion of radiolabeled drug. Within one (1) week, 92% to 98% of the dose was recovered, almost entirely in the urine. Gemcitabine (<10%) and the inactive uracil metabolite, 2´-deoxy-2´,2´-difluorouridine (dFdU), accounted for 99% of the excreted dose. The metabolite dFdU is also found in plasma.

The active metabolite, gemcitabine triphosphate, can be extracted from peripheral blood mononuclear cells. The half-life of the terminal phase for gemcitabine triphosphate from mononuclear cells ranges from 1.7 to 19.4 hours.

Elimination

Clearance of gemcitabine was affected by age and gender. The lower clearance in women and the elderly results in higher concentrations of gemcitabine for any given dose. Differences in either clearance or volume of distribution based on patient characteristics or the duration of infusion result in changes in half-life and plasma concentrations. Table 10 shows plasma clearance and half-life of gemcitabine following short infusions for typical patients by age and gender.

Table 10: Gemcitabine Clearance and Half–Life for the “Typical” Patient

Age | Clearance Men (L/hr/m^2) | Clearance Women (L/hr/m^2) | Half–Lifea Men (min) | Half–Lifea Women (min)
29 | 92.2 | 69.4 | 42 | 49
45 | 75.7 | 57 | 48 | 57
65 | 55.1 | 41.5 | 61 | 73
79 | 40.7 | 30.7 | 79 | 94

aHalf–life for patients receiving < 70 minute infusion.

Gemcitabine half-life for short infusions ranged from 42 to 94 minutes, and the value for long infusions varied from 245 to 638 minutes, depending on age and gender, reflecting a greatly increased volume of distribution with longer infusions.

Drug Interactions

When gemcitabine for injection (1250 mg/m^2 on Days 1 and 8) and cisplatin (75 mg/m^2 on Day 1) were administered in NSCLC patients, the clearance of gemcitabine on Day 1 was 128 L/hr/m^2 and on Day 8 was 107 L/hr/m^2. Analysis of data from metastatic breast cancer patients shows that, on average, gemcitabine for injection has little or no effect on the pharmacokinetics (clearance and half-life) of paclitaxel and paclitaxel has little or no effect on the pharmacokinetics of gemcitabine. Data from NSCLC patients demonstrate that gemcitabine for injection and carboplatin given in combination does not alter the pharmacokinetics of gemcitabine or carboplatin compared to administration of either single-agent. However, due to wide confidence intervals and small sample size, interpatient variability may be observed.

13 NONCLINICAL TOXICOLOGY

13.1 Carcinogenesis, Mutagenesis, Impairment Of Fertility

Long-term animal studies to evaluate the carcinogenic potential of gemcitabine for injection have not been conducted. Gemcitabine was mutagenic in an in vitro mouse lymphoma (L5178Y) assay and was clastogenic in an in vivo mouse micronucleus assay. Gemcitabine IP doses of 0.5 mg/kg/day (about 1/700 the human dose on a mg/m^2 basis) in male mice had an effect on fertility with moderate to severe hypospermatogenesis, decreased fertility, and decreased implantations. In female mice, fertility was not affected but maternal toxicities were observed at 1.5 mg/kg/day administered intravenously (about 1/200 the human dose on a mg/m^2 basis) and fetotoxicity or embryolethality was observed at 0.25 mg/kg/day administered intravenously (about 1/1300 the human dose on a mg/m^2 basis).

14 CLINICAL STUDIES

14.1 Ovarian Cancer

The safety and efficacy of gemcitabine for injection was studied in a randomized trial of 356 women with advanced ovarian cancer that had relapsed at least 6 months after first-line platinum-based therapy. Patients were randomized to receive either gemcitabine for injection 1000 mg/m^2 on Days 1 and 8 of a 21-day cycle and carboplatin AUC 4 administered after gemcitabine for injection infusion on Day 1 of each cycle (n=178) or to carboplatin AUC 5 administered on Day 1 of each 21-day cycle (n=178). The primary efficacy outcome measure was progression free survival (PFS).

Patient characteristics are shown in Table 11. The addition of gemcitabine for injection to carboplatin resulted in statistically significant improvements in PFS and overall response rate as shown in Table 12 and Figure 1. Approximately 75% of patients in each arm received additional chemotherapy for disease progression; 13 of 120 patients in the carboplatin alone arm received gemcitabine for injection for treatment of disease progression. There was no significant difference in overall survival between the treatment arms.

Table 11: Randomized Trial of Gemcitabine For Injection plus Carboplatin versus Carboplatin in Ovarian Cancer - Baseline Demographics and Clinical Characteristics

 | Gemcitabine For Injection/Carboplatin | Carboplatin
Number of randomized patients | 178 | 178
Median age, years | 59 | 58
Range | 36 to 78 | 21 to 81
Baseline ECOG performance status 0 to 1a | 94% | 95%
Disease Status
Evaluable | 8% | 3%
Bidimensionally measurable | 92% | 96%
Platinum–free intervalb
6 to 12 months | 40% | 40%
>12 months | 59% | 60%
First–line therapy
Platinum–taxane combination | 70% | 71%
Platinum–non–taxane combination | 29% | 28%
Platinum monotherapy | 1% | 1%

a 5 patients on gemcitabine for injection plus carboplatin arm and 4 patients on carboplatin arm with no baseline Eastern Cooperative Oncology Group (ECOG) performance status.

b 2 on gemcitabine for injection plus carboplatin arm and 1 on carboplatin arm had platinum-free interval <6 months.

Table 12: Randomized Trial of Gemcitabine For Injection plus Carboplatin versus Carboplatin in Ovarian Cancer - Efficacy Outcomes

 | Gemcitabine For Injection/Carboplatin (N=178) | Carboplatin (N=178)
Progression-free Survival Median (95% CIa) months | 8.6 (8, 9.7) | 5.8 (5.2, 7.1)
Hazard Ratio (95%, C.I.) | 0.72 (0.57, 0.90)
p-valueb | p=0.0038
Overall Survival Median (95% CI) months | 18 (16.2, 20.3) | 17.3 (15.2, 19.3)
Hazard Ratio (95% CI) | 0.98 (0.78, 1.24)
p-valueb | p=0.8977
Investigator Reviewed Overall Response Rate | 47.2% | 30.9%
p-valuee | p=0.0016
CRd PR plus PRNMe | 14.6% 32.6% | 6.2% 24.7%
Independently Reviewed Overall Response Ratef | 46.3% | 35.6%
p-valuee | p=0.11
CRd PR plus PRNMe | 9.1% 37.2% | 4% 31.7%

a CI=confidence interval

b Complete response

c Partial response plus partial response, non-measurable disease

d log Rank, unadjusted

e chi Square

f Independently reviewed cohort –gemcitabine for injection/carboplatin (n=121), carboplatin (n=101); independent reviewers unable to measure disease detected by sonography or physical exam

Figure 1: Kaplan–Meier Curve of Progression Free Survival in Gemcitabine For Injection Plus Carboplatin Versus Carboplatin in Ovarian Cancer (N=356)

14.2 Breast Cancer

The safety and efficacy of gemcitabine for injection were evaluated in a multi-national, randomized, open-label trial conducted in women receiving initial treatment for metastatic breast cancer in women who have received prior adjuvant/neoadjuvant anthracycline chemotherapy unless clinically contraindicated. Patients were randomized to receive gemcitabine for injection 1250 mg/m^2 on Days 1 and 8 of a 21-day cycle and paclitaxel 175 mg/m^2 administered prior to gemcitabine for injection on Day 1 of each cycle (n=267) or to receive paclitaxel 175 mg/m^2 was administered on Day 1 of each 21-day cycle (n=262). The primary efficacy outcome measure was time to documented disease progression.

Table 13: Randomized Trial of Gemcitabine For Injection plus Paclitaxel versus Paclitaxel in Breast Cancer

 | Gemcitabine For Injection/Paclitaxel | Paclitaxel
Number of patients | 267 | 262
Demographic/Entry Characteristics Median age (years) Range | 53 26 to 83 | 52 26 to 75
Metastatic disease | 97% | 97%
Baseline KPSa ≥90 | 70% | 74%
Number of tumor sites 1 to 2 ≥ 3 | 57% 43% | 59% 41%
Visceral disease | 73% | 73%
Prior anthracycline | 97% | 96%
Efficacy Outcomes
Time to Documented Disease Progressionb
Median in months (95% CI) | 5.2 (4.2, 5.6) | 2.9 (2.6, 3.7)
Hazard Ratio (95% CI) | 0.650 (0.524, 0.805)
p-value | p<0.0001
Overall Survivalc
Median Survival in months (95% CI) | 18.6 (16.5, 20.7) | 15.8 (14.1, 17.3)
Hazard Ratio (95% CI) | 0.86 (0.71, 1.04)
p-value | Not Significant
Overall Response Rate (95% CI) | 40.8% (34.9, 46.7) | 22.1% (17.1, 27.2)
p-value | p<0.0001

a Karnofsky Performance Status.

b These represent reconciliation of investigator and Independent Review Committee assessments according to a predefined algorithm. c Based on the ITT population

Figure 2: Kaplan–Meier Curve of Time to Documented Disease Progression in Gemcitabine For Injection Plus Paclitaxel versus Paclitaxel Breast Cancer Study (N=529)

14.3 Non-Small Cell Lung Cancer (NSCLC)

The safety and efficacy of gemcitabine for injection was evaluated in two randomized, multicenter trials.

28-Day Schedule

A multinational, randomized trial compared gemcitabine for injection plus cisplatin to cisplatin alone in the treatment of patients with inoperable Stage IIIA, IIIB, or IV NSCLC who had not received prior chemotherapy. Patients were randomized to receive gemcitabine for injection 1000 mg/m^2 on Days 1, 8, and 15 of a 28-day cycle with cisplatin 100 mg/m^2 administered on Day 1 of each cycle or to receive cisplatin 100 mg/m^2 on Day 1 of each 28-day cycle. The primary efficacy outcome measure was overall survival. A total of 522 patients were enrolled at clinical centers in Europe, the US, and Canada. Patient demographics and baseline characteristics (shown in Table 13) were similar between arms with the exception of histologic subtype of NSCLC, with 48% of patients on the cisplatin arm and 37% of patients on the gemcitabine for injection plus cisplatin arm having adenocarcinoma. Efficacy results are presented in Table 13 and Figure 3 for overall survival.

21-Day Schedule

A randomized (1:1), multicenter trial was conducted in 135 patients with Stage IIIB or IV NSCLC. Patients were randomized to receive gemcitabine for injection 1250 mg/m^2 on Days 1 and 8, and cisplatin 100 mg/m^2 on Day 1 of a 21-day cycle or to receive etoposide 100 mg/m^2 intravenously on Days 1, 2, and 3 and cisplatin 100 mg/m^2 on Day 1 of a 21 -day cycle.

There was no significant difference in survival between the two treatment arms (Log rank p=0.18, two-sided). The median survival was 8.7 months for the gemcitabine for injection plus cisplatin arm versus 7 months for the etoposide plus cisplatin arm. Median time to disease progression for the gemcitabine for injection plus cisplatin arm was 5 months compared to 4.1 months on the etoposide plus cisplatin arm (Log rank p=0.015, two-sided). The objective response rate for the gemcitabine for injection plus cisplatin arm was 33% compared to 14% on the etoposide plus cisplatin arm (Fisher’s Exact p=0.01, two-sided).

Figure 3: Kaplan-Meier Survival Curve in Gemcitabine for injection Plus Cisplatin versus Cisplatin in patients with NSCLC Study (N=522)

Table 14: Randomized Trials of Gemcitabine For Injection plus Cisplatin in Patients with NSCLC

Trial | 28–day Schedulea
Treatment Arm | Gemcitabine For Injection/ Cisplatin | Cisplatin | Gemcitabine For Injection plus Cisplatin | Etoposide plus Cisplatin
Number of patients Demographic/Entry Characteristics | 260 | 262 | 69 | 66
Male | 70% | 71% | 93% | 92%
Median age, years | 62 | 63 | 58 | 60
Range | 36 to 88 | 35 to 79 | 33 to 76 | 35 to 75
Stage IIIA | 7% | 7% | N/Ac | N/Ac
Stage IIIB | 26% | 23% | 48% | 52%
Stage IV | 67% | 70% | 52% | 49%
Baseline KPSd 70 to 80 | 41% | 44% | 45% | 52%
Baseline KPSd 90 to 100 | 57% | 55% | 55% | 49%
Efficacy Outcomes
Survival
Median in months | 9 | 7.6 | 8.7 | 7
(95%, C.Ie) months | 8.2, 11 | 6.6, 8.8 | 7.8, 10.1 | 6, 9.7
p-valuef | p=0.008 |  | p=0.18
Time to Disease Progression
Median in months | 5.2 | 3.7 | 5 | 4.1
(95%, C.Ie) months | 4.2, 5.7 | 3, 4.3 | 4.2, 6.4 | 2.4, 4.5
p-valuef | p=0.009 |  | p=0.015
Tumor Response | 26% | 10% | 33% | 14%
p-valuef | p<0.0001 |  | p=0.01%

a 28–day schedule — Gemcitabine for injection plus cisplatin: Gemcitabine for injection 1000 mg/m^2 on Days 1, 8, and 15 and cisplatin 100 mg/m^2 on Day 1 every 28 days; Single–agent cisplatin: cisplatin 100 mg/m^2 on Day 1 every 28 days.

b 21–day schedule — Gemcitabine for injection plus cisplatin: Gemcitabine for injection 1250 mg/m^2 on Days 1 and 8 and cisplatin 100 mg/m^2 on Day 1 every 21 days; Etoposide plus Cisplatin: cisplatin 100 mg/m^2 on Day 1 and intravenous etoposide 100 mg/m^2 on Days 1, 2, and 3 every 21 days.

c N/A Not applicable

d Karnofsky Performance Status.

e CI=confidence intervals

f p-value two-sided Fisher’s Exact test for difference in binomial proportions; log rank test for time-to-event analyses.

14.4 Pancreatic Cancer

The safety and efficacy of gemcitabine for injection was evaluated in two trials, a randomized, single-blind, two-arm, active-controlled trial conducted in patients with locally advanced or metastatic pancreatic cancer who had received no prior chemotherapy and in a single-arm, open-label, multicenter trial conducted in patients with locally advanced or metastatic pancreatic cancer previously treated with 5-FU or a 5-FU-containing regimen. The first trial randomized patients to receive gemcitabine for injection 1000 mg/m^2 intravenously over 30 minutes once weekly for 7 weeks followed by a one-week rest, then once weekly dosing for 3 consecutive weeks every 28-days in subsequent cycles (n=63) or to 5-fluorouracil (5-FU) 600 mg/m^2 intravenously over 30 minutes once weekly (n=63). In the second trial, all patients received gemcitabine for injection 1000 mg/m^2 intravenously over 30 minutes once weekly for 7 weeks followed by a one-week rest, then once weekly dosing for 3 consecutive weeks every 28-days in subsequent cycles.

The primary efficacy outcome measure in both trials was "clinical benefit response". A patient was considered to have had a clinical benefit response if either occurred:

The patient achieved a ≥50% reduction in pain intensity (Memorial Pain Assessment Card) or analgesic consumption, or a 20-point or greater improvement in performance status (Karnofsky Performance Status) for a period of at least 4 consecutive weeks, without showing any sustained worsening in any of the other parameters. Sustained worsening was defined as 4 consecutive weeks with either any increase in pain intensity or analgesic consumption or a 20-point decrease in performance status occurring during the first 12 weeks of therapy.

OR

The patient was stable on all of the aforementioned parameters, and showed a marked, sustained weight gain (≥7% increase maintained for ≥4 weeks) not due to fluid accumulation.

The randomized trial enrolled 126 patients across 17 sites in the US and Canada. The demographic and entry characteristics were similar between the arms (Table 15). The efficacy outcome results are shown in Table 15 and for overall survival in Figure 4. Patients treated with gemcitabine for injection had statistically significant increases in clinical benefit response, survival, and time to disease progression compared to those randomized to receive 5-FU. No confirmed objective tumor responses were observed in either treatment arm.

Table 15: Randomized Trial of Gemcitabine For Injection versus 5-Fluorouracil in Pancreatic Cancer

 | Gemcitabine For Injection | 5–FU
Number of patients | 63 | 63
Demographic/Entry Characteristics
Male | 54% | 54%
Median age | 62 years | 61 years
Range | 37 to 79 | 36 to 77
Stage IV disease | 71% | 76%
Baseline KPSa ≤ 70 | 70% | 68%
Efficacy Outcomes
Clinical benefit response | 22.2% | 4.8%
p-valueb | p=0.004
Survival
Median | 5.7 months | 4.2 months
(95% CI) | (4.7, 6.9) | (3.1, 5.1)
p-valueb | p=0.0009
Time Disease Progression
Median | 2.1 months | 0.9 months
(95% CI) | (1.9, 3.4) | (0.9, 1.1)
p-value b | p=0.0013

a Karnofsky Performance Status.

b p-value for clinical benefit response calculated using the two-sided test for difference in binomial proportions. All other p-values are calculated using log rank test.

Figure 4: Kaplan-Meier Survival Curve

16 HOW SUPPLIED/STORAGE AND HANDLING

16.1 How Supplied

Gemcitabine for Injection, USP is available in sterile single-use vials individually packaged in a carton containing:

200 mg white, lyophilized powder in a sterile single-use vial - NDC 55390-391-10.

1 g white, lyophilized powder in a sterile single-use vial – 55390-391-50.

16.2 Storage and Handling

Unopened vials of gemcitabine for injection are stable until the expiration date indicated on the package when stored at 20° to 25°C (68° to 77°F); [See USP Controlled Room Temperature]. [see Dosage and Administration (2.5 and 2.6)].

17 PATIENT COUNSELING INFORMATION

- Advise patients of the risks of low blood cell counts and the potential need for blood transfusions and increased susceptibility to infections. Instruct patients to immediately contact their healthcare provided for development of signs or symptoms of infection, fever, prolonged or unexpected bleeding, bruising, or shortness of breath [see Warnings and Precautions (5.2)]
- Advise patients of the risks of pulmonary toxicity including respiratory failure and death. Instruct patients to immediately contact their healthcare provider for development of shortness of breath, wheezing, or cough [see Warnings and Precautions (5.3)]
- Advise patients of the risks of hemolytic-uremic syndrome and associated renal failure. Instruct patients to immediately contact their healthcare provider for changes in the color or volume of urine output or for increased bruising or bleeding [see Warnings and Precautions (5.4)]
- Advise patients of the risks of hepatic toxicity including liver failure and death. Instruct patients to immediately contact their healthcare provider for signs of jaundice or for pain/tenderness in the right upper abdominal quadrant [see Warnings and Precautions (5.5)]

Rx Only

Manufactured by:

Dr. Reddy’s Laboratories Limited

Visakhapatnam - 530 046 INDIA

Distributed by:

Bedford Laboratories

TM Bedford, OH 44146

or

Manufactured for:

Dr. Reddy’s Laboratories Limited

BachupallY – 500 090 INDIA

Distributed by:

Bedford LaboratoriesTM

Bedford, OH 44146

Made in India

Revised: 0514

PACKAGE LABEL.PRINCIPAL DISPLAY PANEL SECTION

200 mg Vial Label

PACKAGE LABEL

200 mg Vial Carton

PACKAGE LABEL

1 g Vial

PACKAGE LABEL

1 g Vial Carton